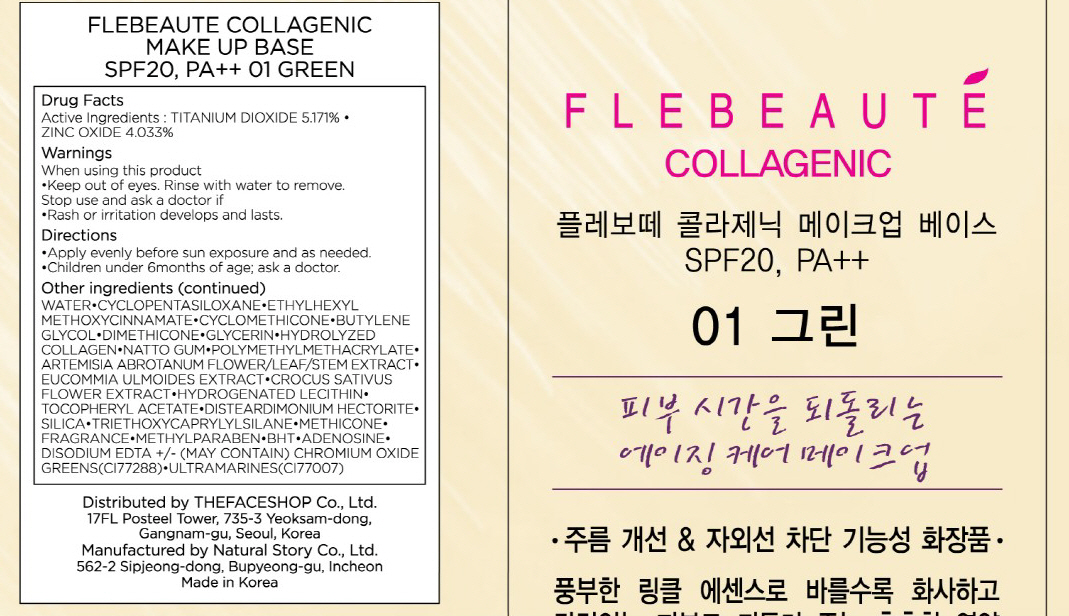 DRUG LABEL: FLEBEAUTE COLLAGENIC MAKE UP BASE
NDC: 51523-006 | Form: CREAM
Manufacturer: THEFACESHOP CO., LTD.
Category: otc | Type: HUMAN OTC DRUG LABEL
Date: 20100713

ACTIVE INGREDIENTS: TITANIUM DIOXIDE 1.81 mL/35 mL; ZINC OXIDE 1.41 mL/35 mL

Drug Facts

Active Ingredients: TITANIUM DIOXIDE, ZINC OXIDE

Inactive Ingredients:
WATER, CYCLOPENTASILOXANE, ETHYLHEXYL METHOXYCINNAMATE, CYCLOMETHICONE, BUTYLENE GLYCOL, DIMETHICONE, GLYCERIN, HYDROLYZED COLLAGEN, NATTO GUM, POLYMETHYLMETHACRYLATE, ARTEMISIA ABROTANUM FLOWER/LEAF/STEM EXTRACT, EUCOMMIA ULMOIDES EXTRACT, CROCUS SATIVUS FLOWER EXTRACT,
HYDROGENATED LECITHIN, TOCOPHERYL ACETATE, DISTEARDIMONIUM HECTORITE, SILICA, TRIETHOXYCAPRYLYLSILANE, METHICONE, FRAGRANCE, METHYLPARABEN,
BHT, ADENOSINE, DISODIUM EDTA
(MAY CONTAIN) CHROMIUM OXIDE GREENS(CI77288), ULTRAMARINES(CI77007)

Warnings:
When using this product
Keep out of eyes. Rinse with water to remove.
Stop use and ask a doctor if
Rash or irritation develops and lasts.
Directions:
Apply evenly before sun exposure and as needed.
Children under 6months of age; ask a doctor.